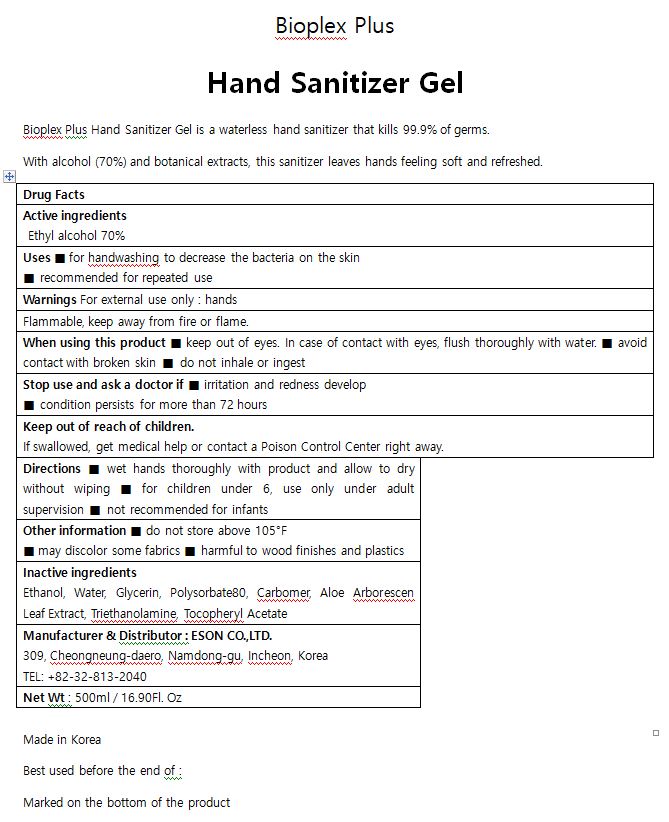 DRUG LABEL: Bioplex Plus Hand Sanitizer gel
NDC: 76677-0003 | Form: GEL
Manufacturer: ESON
Category: otc | Type: HUMAN OTC DRUG LABEL
Date: 20200518

ACTIVE INGREDIENTS: ALCOHOL 70 mL/100 mL
INACTIVE INGREDIENTS: ALOE VERA LEAF; GLYCERIN; POLYSORBATE 80; .ALPHA.-TOCOPHEROL ACETATE; CARBOMER 940; TROLAMINE; WATER

Drug Facts

ACTIVE INGREDIENT

alcohol

INACTIVE INGREDIENT

Water, Glycerin, Polysorbate80, Carbomer, Aloe Barbadensis Leaf Extract, Triethanolamine, Tocopheryl Acetate

PURPOSE

Sterilization of hands and skin

KEEP OUT OF REACH OF THE CHILDREN

INDICATIONS AND USAGE

Apply to clean, dry hands. Apply sufficient amount to thoroughly wet all surfaces of hands and fingers. Rub onto hands until dry.

Supervise children in the use of this product.

WARNINGS

■ Flammable. Keep away from fire or flame.

■ For external use only.

■ Do not use in eyes.

■ lf swallowed, get medical help promptly.

■ Stop use, ask doctor lf irritation occurs.

■ Keep out of reach of children.

DOSAGE AND ADMINISTRATION

for external use only